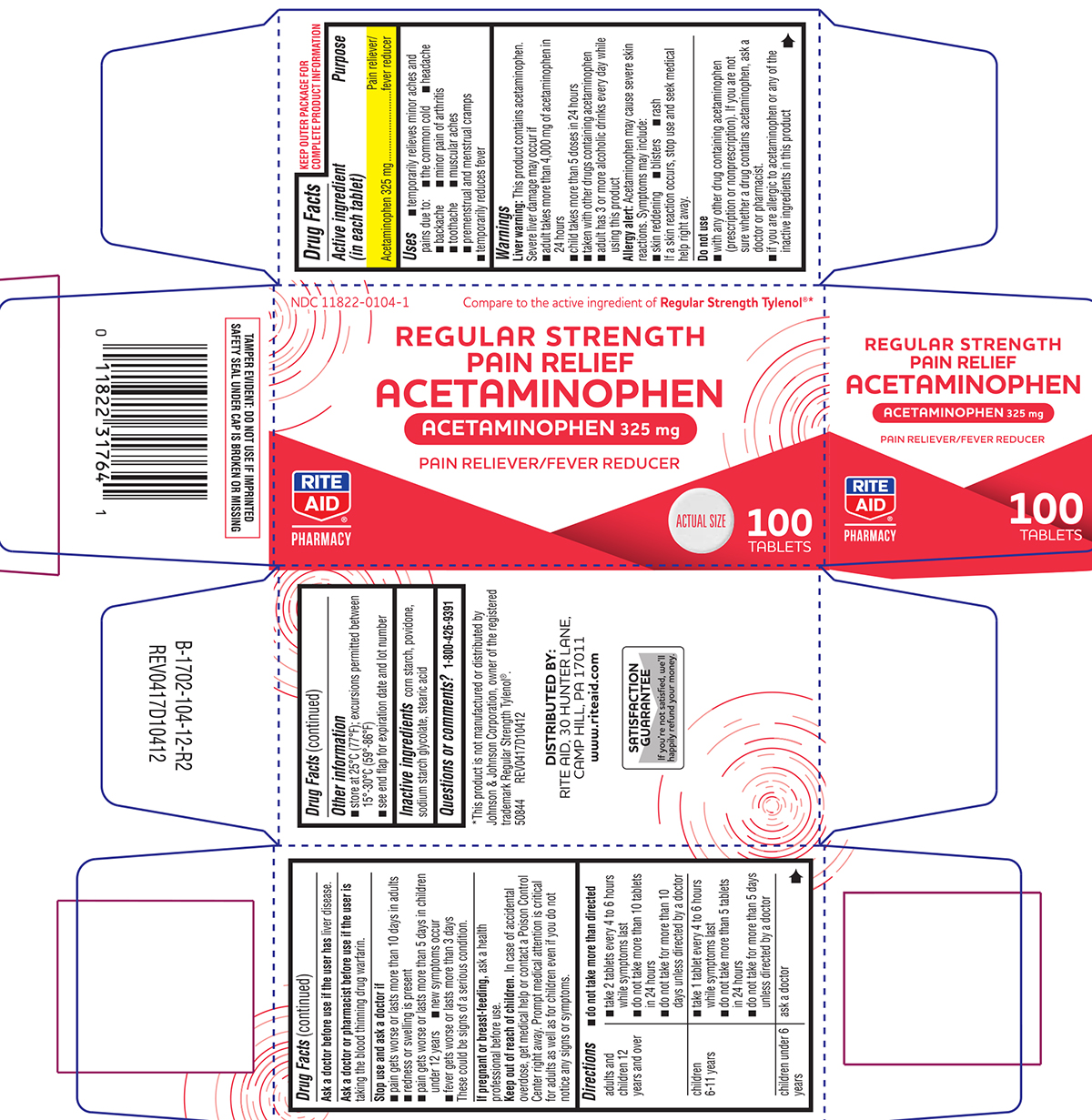 DRUG LABEL: Pain Relief
NDC: 11822-0104 | Form: TABLET
Manufacturer: Rite Aid Corporation
Category: otc | Type: HUMAN OTC DRUG LABEL
Date: 20250811

ACTIVE INGREDIENTS: ACETAMINOPHEN 325 mg/1 1
INACTIVE INGREDIENTS: STARCH, CORN; POVIDONE, UNSPECIFIED; SODIUM STARCH GLYCOLATE TYPE A POTATO; STEARIC ACID

Rite Aid 44-104

Active ingredient (in each tablet)

Acetaminophen 325 mg

Purpose

Pain reliever/fever reducer

Uses

- temporarily relieves minor aches and pains due to:
  - the common cold
  - headache
  - backache
  - minor pain of arthritis
  - toothache
  - muscular aches
  - premenstrual and menstrual cramps
- temporarily reduces fever

Warnings

Liver warning: This product contains acetaminophen. Severe liver damage may occur if

- adult takes more than 4,000 mg of acetaminophen in 24 hours
- child takes more than 5 doses in 24 hours
- taken with other drugs containing acetaminophen
- adult has 3 or more alcoholic drinks every day while using this product

Allergy alert: Acetaminophen may cause severe skin reactions. Symptoms may include:

- skin reddening
- blisters
- rash

If a skin reaction occurs, stop use and seek medical help right away.

Do not use

- with any other drug containing acetaminophen (prescription or nonprescription). If you are not sure whether a drug contains acetaminophen, ask a doctor or pharmacist.
- if you are allergic to acetaminophen or any of the inactive ingredients in this product

Ask a doctor before use if the user has

liver disease.

Ask a doctor or pharmacist before use if the user is

taking the blood thinning drug warfarin.

Stop use and ask a doctor if

- pain gets worse or lasts more than 10 days in adults
- redness or swelling is present
- pain gets worse or lasts more than 5 days in children under 12 years
- new symptoms occur
- fever gets worse or lasts more than 3 days

These could be signs of a serious condition.

If pregnant or breast-feeding,

ask a health professional before use.

Keep out of reach of children.

In case of accidental overdose, get medical help or contact a Poison Control Center right away. Prompt medical attention is critical for adults as well as for children even if you do not notice any signs or symptoms.

Directions

- do not take more than directed

adults and children 12 years and over | - take 2 tablets every 4 to 6 hours while symptoms last - do not take more than 10 tablets in 24 hours - do not take for more than 10 days unless directed by a doctor
children 6-11 years | - take 1 tablet every 4 to 6 hours while symptoms last - do not take more than 5 tablets in 24 hours - do not take for more than 5 days unless directed by a doctor
children under 6 years | ask a doctor

Other information

- store at 25°C (77°F); excursions permitted between 15°-30°C (59°-86°F)
- see end flap for expiration date and lot number

Inactive ingredients

corn starch, povidone, sodium starch glycolate, stearic acid

Questions or comments?

1-800-426-9391

Principal Display Panel

NDC 11822-0104-1

Compare to the active ingredient of Regular Strength Tylenol®*

REGULAR STRENGTH
PAIN RELIEF
ACETAMINOPHEN

ACETAMINOPHEN 325 mg

PAIN RELIEVER/FEVER REDUCER

RITE
AID®
PHARMACY

ACTUAL SIZE

100 TABLETS

*This product is not manufactured or distributed by
Johnson & Johnson Corporation, owner of the registered
trademark Regular Strength Tylenol®.
50844 REV0417D10412

DISTRIBUTED BY:
RITE AID, 30 HUNTER LANE,
CAMP HILL, PA 17011
www.riteaid.com

SATISFACTION
GUARANTEE
If you're not satisfied, we'll
happily refund your money.

TAMPER EVIDENT: DO NOT USE IF IMPRINTED
SAFETY SEAL UNDER CAP IS BROKEN OR MISSING

Rite Aid 44-104